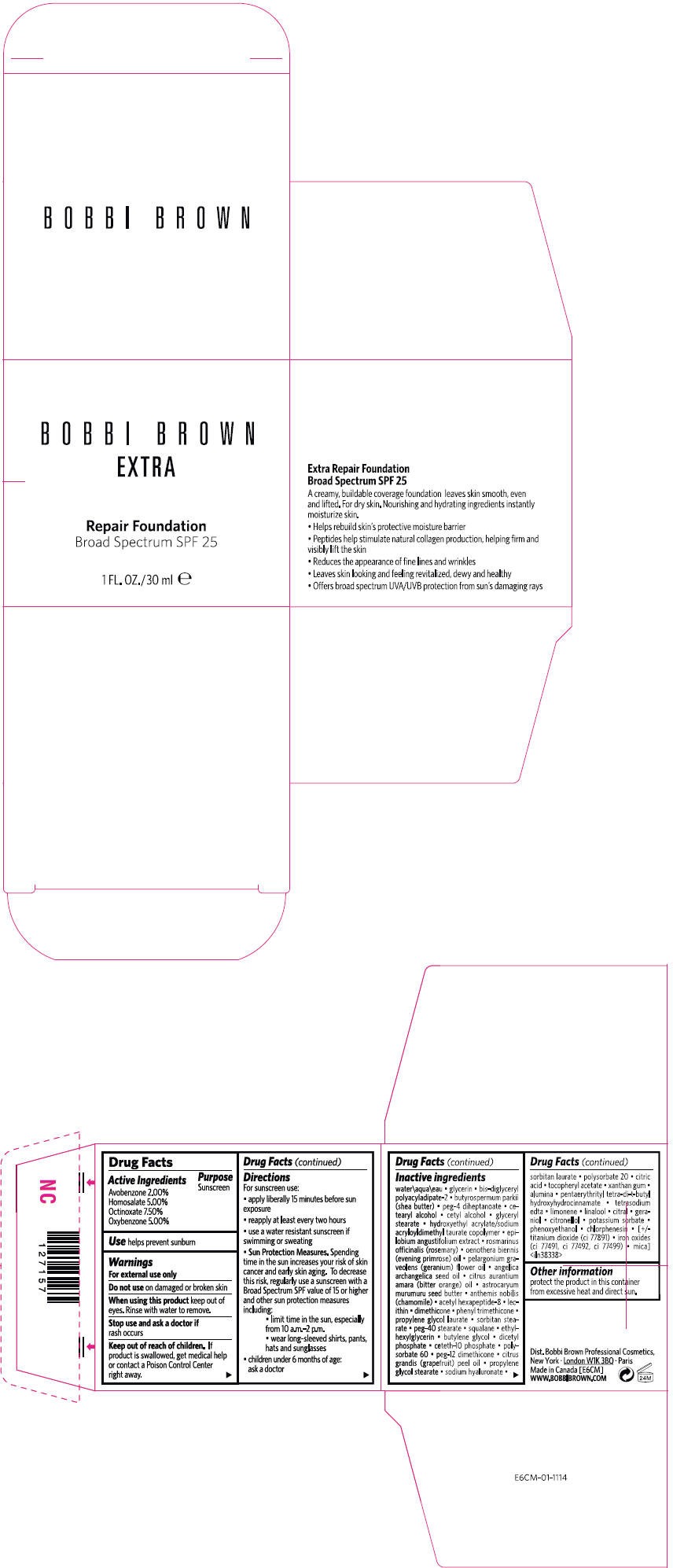 DRUG LABEL: EXTRA REPAIR FOUNDATION
NDC: 64141-008 | Form: CREAM
Manufacturer: Bobbi Brown Professional Cosmetics Inc.
Category: otc | Type: HUMAN OTC DRUG LABEL
Date: 20120406

ACTIVE INGREDIENTS: OCTINOXATE 7.5 mL/100 mL; HOMOSALATE 5.0 mL/100 mL; OXYBENZONE 5.0 mL/100 mL; AVOBENZONE 2.0 mL/100 mL
INACTIVE INGREDIENTS: WATER; SHEA BUTTER; GLYCERIN; CETOSTEARYL ALCOHOL; CETYL ALCOHOL; GLYCERYL MONOSTEARATE; GERANIUM OIL, ALGERIAN TYPE; EVENING PRIMROSE OIL; ASTROCARYUM MURUMURU SEED BUTTER; CARROT; CHAMAEMELUM NOBILE; LECITHIN, SOYBEAN; DIMETHICONE; SORBITAN MONOSTEARATE; SQUALANE; BUTYLENE GLYCOL; POLYSORBATE 60; PROPYLENE GLYCOL MONOPALMITOSTEARATE; SORBITAN MONOLAURATE; POLYSORBATE 20; CITRIC ACID MONOHYDRATE; POTASSIUM SORBATE; PHENOXYETHANOL

BOBBI BROWN
EXTRA
Repair Foundation
Broad Spectrum SPF 25

Drug Facts

Active Ingredients

Avobenzone 2.00%
Homosalate 5.00%
Octinoxate 7.50%
Oxybenzone 5.00%

Purpose

Sunscreen

Use

helps prevent sunburn

Warnings

For external use only

Do not use on damaged or broken skin

When using this product keep out of eyes. Rinse with water to remove.

Stop use and ask a doctor if rash oocurs

Keep out of reach of children. If product is swallowed, get medical help or contact a Poison Control Center right away.

Directions

For sunscreen use:

- apply liberally 15 minutes before sun exposure
- reapply at least every two hours
- use a water resistant sunscreen if swimming or sweating
- Sun Protection Measures. Spending time in the sun increases your risk of skin cancer and early skin aging. To decrease this risk, regulary use a sunscreen with a Broad Spectrum SPF value of 15 or higher and other sun protection measures including:
  - limit time in the sun, especially from 10 a.m.-2 p.m.
  - wear long-sleezed shirts, pants, hats and sunglasses
- children under 6 months of age: ask a doctor

Inactive ingredients

water\aqua\eau • glycerin • bis-diglyceryl polyacyladipate-2 • butyrospermum parkii (shea butter) • peg-4 diheptanoate • cetearyl alcohol • cetyl alcohol • glyceryl stearate • hydroxyethyl acrylate/sodium acryloyldimethyl taurate copolymer • epilobium angustifolium extract • rosmarinus officinalis (rosemary) • oenothera biennis (evening primrose) oil • pelargonium graveolens (geranium) flower oil • angelica archangelica seed oil • citrus aurantium amara (bitter orange) oil • astrocaryum murumuru seed butter • anthemis nobilis (chamomile) • acetyl hexapeptide-8 • lecithin • dimethicone • phenyl trimethicone • propylene glycol laurate • sorbitan stearate • peg-40 stearate • squalane • ethylhexylglycerin • butylene glycol • dicetylphosphate • ceteth-10 phosphate • polysorbate 60 • peg-12 dimethicone • citrus grandis (grapefruit) peel oil • propylene glycol stearate • sodium hyaluronate • sorbitan laurate • polysorbate 20 • citric acid • tocopheryl acetate • xanthan gum • alumina • pentaerythrityl tetra-di-t-butyl hydroxyhydrocinnamate • tetrasodium edta • limonene • linalool • citral • geraniol • citronellol • potassium sorbate • phenoxyethanol • chlorphenesin • [+/- titanium dioxide (ci 77891) • iron oxides (ci 77491, ci 77492, ci 77499) • mica]<iln38338>

Other information

protect the product in this container from excessive heat and direct sun.

Dist. Bobbi Brown Professional Cosmetics,
New York

PRINCIPAL DISPLAY PANEL - 30 ml Jar Carton

BOBBI BROWN
EXTRA

Repair Foundation
Broad Spectrum SPF 25

1 FL. OZ./30 ml e